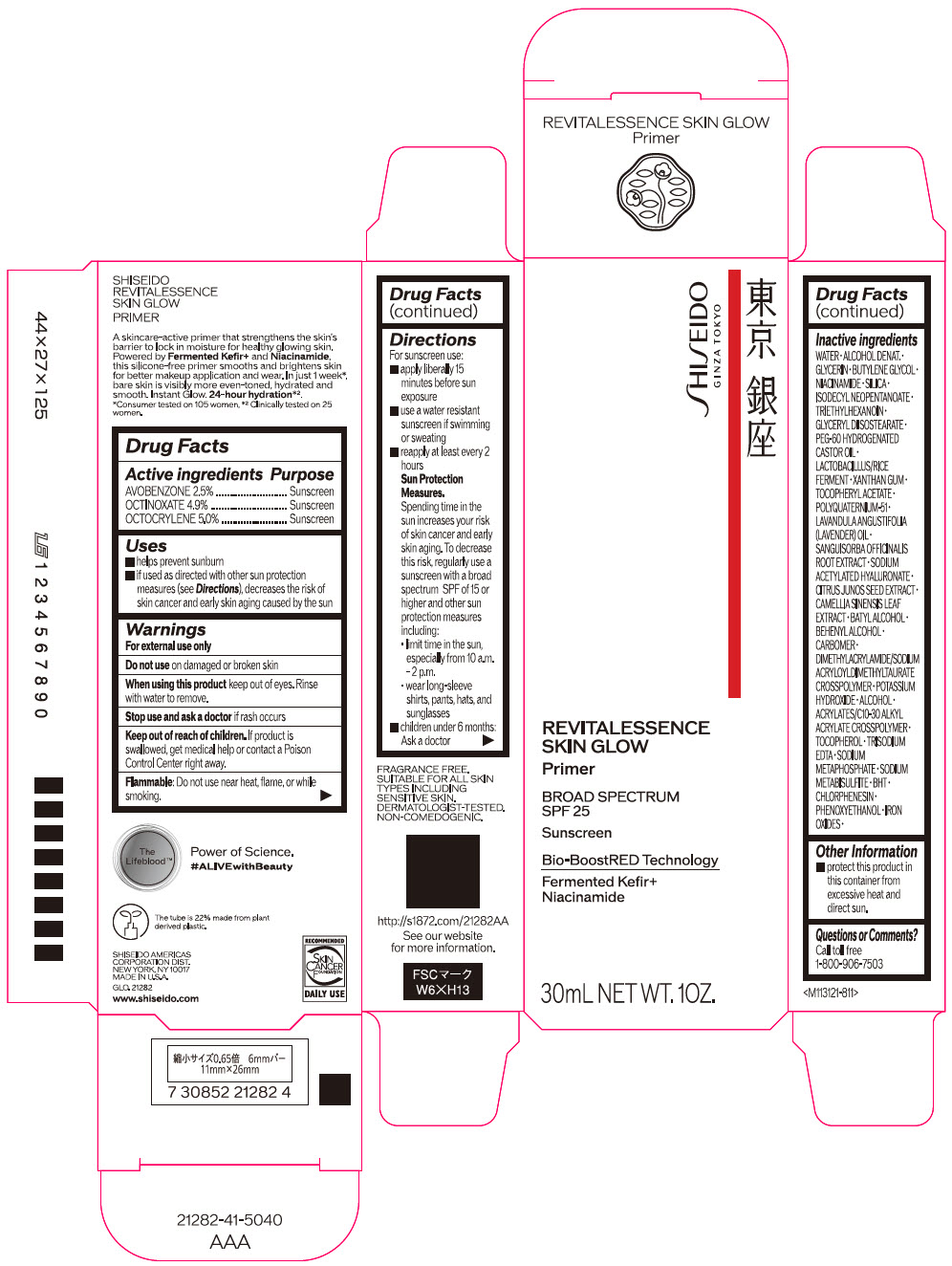 DRUG LABEL: SHISEIDO REVITALESSENCE SKIN GLOW PRIMER
NDC: 58411-894 | Form: EMULSION
Manufacturer: SHISEIDO AMERICAS CORPORATION
Category: otc | Type: HUMAN OTC DRUG LABEL
Date: 20250313

ACTIVE INGREDIENTS: AVOBENZONE 0.77925 g/30 mL; OCTINOXATE 1.52733 g/30 mL; OCTOCRYLENE 1.5585 g/30 mL
INACTIVE INGREDIENTS: WATER; GLYCERIN; BUTYLENE GLYCOL; NIACINAMIDE; SILICON DIOXIDE; ISODECYL NEOPENTANOATE; TRIETHYLHEXANOIN; GLYCERYL DIISOSTEARATE; PEG-60 HYDROGENATED CASTOR OIL; LIMOSILACTOBACILLUS REUTERI; XANTHAN GUM; .ALPHA.-TOCOPHEROL ACETATE, DL-; POLYQUATERNIUM-51 (2-METHACRYLOYLOXYETHYL PHOSPHORYLCHOLINE/N-BUTYL METHACRYLATE; 3:7); LAVENDER OIL; SANGUISORBA OFFICINALIS ROOT; SODIUM ACETYLATED HYALURONATE; CITRUS JUNOS SEED; GREEN TEA LEAF; BATILOL; DOCOSANOL; CARBOMER HOMOPOLYMER, UNSPECIFIED TYPE; POTASSIUM HYDROXIDE; ALCOHOL; ACRYLATES/C10-30 ALKYL ACRYLATE CROSSPOLYMER (60000 MPA.S); .ALPHA.-TOCOPHEROL; EDETATE TRISODIUM; SODIUM METAPHOSPHATE; SODIUM METABISULFITE; BUTYLATED HYDROXYTOLUENE; CHLORPHENESIN; PHENOXYETHANOL; FERRIC OXIDE RED; FERRIC OXIDE YELLOW; FERROSOFERRIC OXIDE

SHISEIDO REVITALESSENCE SKIN GLOW PRIMER

Drug Facts

ACTIVE INGREDIENT

Active ingredients | Purpose
AVOBENZONE 2.5% | Sunscreen
OCTINOXATE 4.9% | Sunscreen
OCTOCRYLENE 5.0% | Sunscreen

Uses

- helps prevent sunburn
- if used as directed with other sun protection measures (see Directions), decreases the risk of skin cancer and early skin aging caused by the sun

Warnings

For external use only

Do not use on damaged or broken skin

When using this product keep out of eyes. Rinse with water to remove.

Stop use and ask a doctor if rash occurs.

Keep out of reach of children. If product is swallowed, get medical help or contact a Poison Control Center right away.

Directions

For sunscreen use:

- apply liberally 15 minutes before sun exposure
- use a water resistant sunscreen if swimming or sweating
- reapply at least every 2 hours
- Sun Protection Measures. Spending time in the sun increases your risk of skin cancer and early skin aging. To decrease this risk, regularly use a sunscreen with a Broad Spectrum SPF of 15 or higher and other sun protection measures including:
  - limit time in the sun, especially from 10 a.m. – 2 p.m.
  - wear long-sleeve shirts, pants, hats, and sunglasses
- children under 6 months: Ask a doctor

Inactive Ingredients

WATER･ALCOHOL DENAT.･GLYCERIN･BUTYLENE GLYCOL･NIACINAMIDE･SILICA･ISODECYL NEOPENTANOATE･TRIETHYLHEXANOIN･GLYCERYL DIISOSTEARATE･PEG-60 HYDROGENATED CASTOR OIL･LACTOBACILLUS/RICE FERMENT･XANTHAN GUM･TOCOPHERYL ACETATE･POLYQUATERNIUM-51･LAVANDULA ANGUSTIFOLIA (LAVENDER) OIL･SANGUISORBA OFFICINALIS ROOT EXTRACT･SODIUM ACETYLATED HYALURONATE･CITRUS JUNOS SEED EXTRACT･CAMELLIA SINENSIS LEAF EXTRACT･BATYL ALCOHOL･BEHENYL ALCOHOL･CARBOMER･DIMETHYLACRYLAMIDE/SODIUM ACRYLOYLDIMETHYLTAURATE CROSSPOLYMER･POTASSIUM HYDROXIDE･ALCOHOL･ACRYLATES/C10-30 ALKYL ACRYLATE CROSSPOLYMER･TOCOPHEROL･TRISODIUM EDTA･SODIUM METAPHOSPHATE･SODIUM METABISULFITE･BHT･CHLORPHENESIN･PHENOXYETHANOL･IRON OXIDES･

Other information

- protect this product in this container from excessive heat and direct sun.

Questions or comments?

Call toll free 1-800-906-7503

PRINCIPAL DISPLAY PANEL - 30 mL Bottle Carton

SHISEIDO
GINZA TOKYO

REVITALESSENCE
SKIN GLOW

Primer

BROAD SPECTRUM
SPF 25

Sunscreen

Bio-BoostRED Technology

Fermented Kefir+
Niacinamide

30mL NET WT. 10Z.